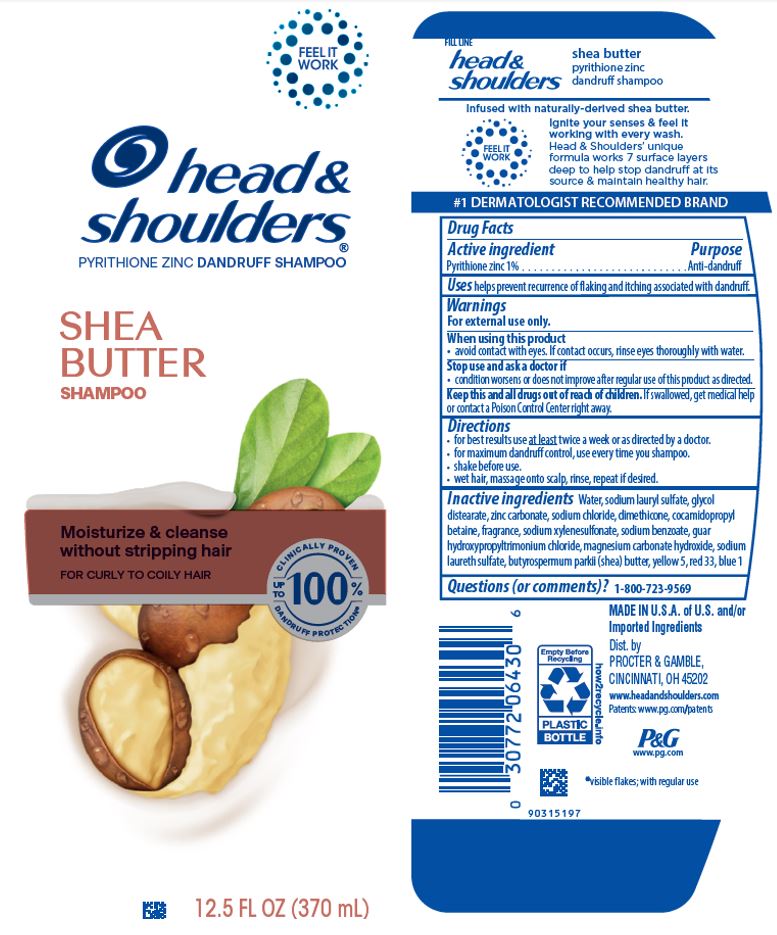 DRUG LABEL: Head and Shoulders Shea Butter
NDC: 69423-671 | Form: SHAMPOO
Manufacturer: The Procter & Gamble Manufacturing Company
Category: otc | Type: HUMAN OTC DRUG LABEL
Date: 20251231

ACTIVE INGREDIENTS: PYRITHIONE ZINC 1 g/100 mL
INACTIVE INGREDIENTS: SODIUM LAURETH SULFATE; FD&C BLUE NO. 1; GUAR HYDROXYPROPYLTRIMONIUM CHLORIDE (1.7 SUBSTITUENTS PER SACCHARIDE); FD&C YELLOW NO. 5; SHEA BUTTER; SODIUM LAURYL SULFATE; WATER; DIMETHICONE; ZINC CARBONATE; GLYCOL DISTEARATE; SODIUM XYLENESULFONATE; COCAMIDOPROPYL BETAINE; SODIUM CHLORIDE; SODIUM BENZOATE; MAGNESIUM CARBONATE HYDROXIDE; D&C RED NO. 33

Head and Shoulders® Shea Butter Shampoo

Drug Facts

Active ingredient

Pyrithione zinc 1%

Purpose

Anti-dandruff

Uses

helps prevent recurrence of flaking and itching associated with dandruff.

Warnings

For external use only.

When using this product

- avoid contact with eyes. If contact occurs, rinse eyes thoroughly with water.

Stop use and ask a doctor if

- condition worsens or does not improve after regular use of this product as directed.

KEEP OUT OF REACH OF CHILDREN

Keep this and all drugs out of reach of children. If swallowed, get medical help or contact a Poison Control Center right away.

Directions

- for best results use at least twice a week or as directed by a doctor.
- for maximum dandruff control, use every time you shampoo.
- shake before use.
- wet hair, massage onto scalp, rinse, repeat if desired.

Inactive ingredients

Water, sodium lauryl sulfate, glycol distearate, zinc carbonate, sodium chloride, dimethicone, cocamidopropyl betaine, fragrance, sodium xylenesulfonate, sodium benzoate, guar hydroxypropyltrimonium chloride, magnesium carbonate hydroxide, sodium laureth sulfate, butyrospermum parkii (shea) butter, yellow 5, red 33, blue 1

Questions (or comments)?

1-800-723-9569

MADE IN U.S.A. of U.S. and/or Imported Ingredients

Dist. by PROCTER & GAMBLE,
CINCINNATI, OH 45202

PRINCIPAL DISPLAY PANEL - 370 mL Bottle Label

head &
shoulders ®

PYRITHIONE ZINC DANDRUFF SHAMPOO

SHEA BUTTER

SHAMPOO

Moisturize & cleanse

without stripping hair

FOR CURLY TO COILY HAIR

12.5 FL OZ (370 mL)